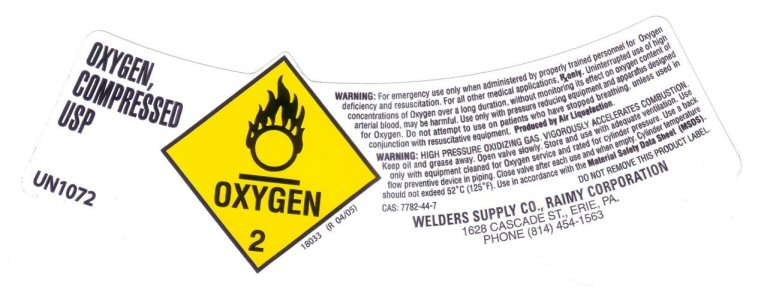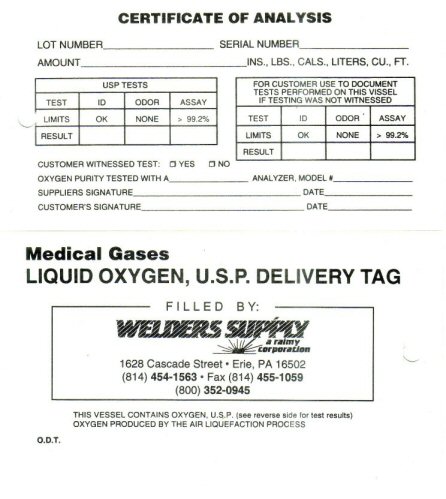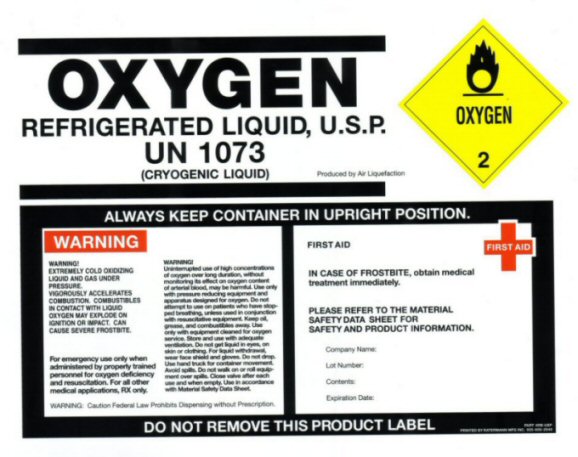 DRUG LABEL: OXYGEN
NDC: 10942-1094 | Form: GAS
Manufacturer: Welders Supply - Raimy Corporation
Category: prescription | Type: HUMAN PRESCRIPTION DRUG LABEL
Date: 20100101

ACTIVE INGREDIENTS: OXYGEN 99 L/100 L

OXYGEN CERTIFICATE OF ANALYSIS

Delivery Tag
CERTIFICATE OF ANALYSIS
Lot Number ________ Serial Number_______ Amount ___________________ INS., LBS., CALS., Liters, CU., FT.
USP Tests
Test ID – ODOR – ASSAY
LIMITS OK – NONE – 99.2%
RESULT
FOR CUSTOMER USE TO DOCUMENT TESTS PERFORMED ON THIS VESSEL IF TESTING WAS NOT WITNESSED
Test ID – ODOR – ASSAY
LIMITS OK – NONE – 99.2%
RESULT
CUSTOMER WITNESSED TEST YES__ NO __ OXYGEN PURITY TESTED WITH A ______ ANALYZER MODEL #___________ SUPPLIERS SIGNATURE _____________________ DATE____
CUSTOMERS SIGNATURE ________________________ DATE_________
MEDICAL GASES
LIQUID OXYGEN, U.S.P. DELIVERY TAG
FILLED BY
WELDERS SUPPLY A RAIMY CORPORATION
1628 CASCADE STREET – ERIE, PA 16502
(814) 454-1563 – FAX (814) 455-1059
(800) 352-0945
THIS VESSEL CONTAINS OXYGEN USP (see reverse side for test results)
OXYGEN PRODUCED BY THE AIR LIQUEFACTION PROCESS
O.D.T.

OXYGEN COMPRESSED LABEL

OXYGEN COMPRESSED USP
UN1072 OXYGEN 2
WARNING: For emergency use only when administered by properly trained personnel for Oxygen deficiency and resuscitation. For all other medical applications Rx Only. Uninterrupted use of high
concentrations of Oxygen over a long duration, without monitoring its effect on oxyen content of arterial blood may be harmful.
Use only with pressure reducing equipment and apparatus designed for Oxygen. Do not attempt to use on patients who have stopped breathing, unless
used in conjunction with resuscitative equipment. PRODUCED BY AIR LIQUEFACTION.
Warning: HIGH PRESSURE OXIDIZING GAS. VIGOROUSLY ACCELERATED COMBUSTION. Keep oil and grease away.
Open valve slowly. Store and use with adequate ventilation. Use only with equipment cleaned for Oxygen Service
and rated for cylinder pressure. Use a back flow preventative device in piping. Close valve after each use and when empty.
Cylinder temperature should not exceed 52 C (125 F) Use in accordance with the Material Safety Data Sheet (MSDS)
CAS 7782-44-7
Do Not Remove this Product Label
18033 (R 04/05)
WELDERS SUPPLY CO. , RAIMY CORPORATION
1628 CASCADE ST. ERIE, PA
PHONE (814) 454-1563

OXYGEN REFRIGERATED LIQUID LABEL

OXYGEN REFRIGERATED LIQUID, U.S.P.
UN 1073 (CRYOGENIC LIQUID)
Produced by Air Liquefaction
OXYGEN 2
ALWAYS KEEP CONTAINER IN UPRIGHT POSITION
For emergency use only when administered by properly trained personnel for oxygen deficiency and resuScitation. For all other medical applications RX only.
Warning: Caution Federal Law Prohibits Dispensing without Prescription.
First Aid IN CASE OF FROSTBITE, obtain medical treatment immediately.
PLEASE REFER TO THE MATERIAL SAFETY DATA SHEET FOR SAFETY AND PRODUCT INFORMATION.
WARNING! EXTREMELY COLD OXIDIZING LIQUID AND GAS UNDER PRESSURE. VIGOROUSLY ACCELERATES COMBUSTION.
COMBUSTIBLES IN CONTACT WITH LIQUID OXYGEN MAY EXPLODE ON IGNITION OR IMPACT. CAN CAUSE SEVERE FROSTBITE.
WARNING! Uninterupted use of high concentrations of oxygen over long duration, without
monitoring its effect on oxygen content of arterial blood, may be harmful. Use only with pressure reducing equipment
and apparatus designed for oxygen. Do not attempt to use on patients who have stopped breathing, unless used in conjunction
with resucitative equipment. Keep oil, grease, and combustibles away. Use only with equipment cleaned for oxygen service. Store and use with adequate
ventilation. Do not get liquid ineyes, on skin or clothing. For liquid withdrawal, wear face shield and gloves. Do not drop. Use hand truck for
container movement. Avoid spills. Do not walk on or roll equipment over spills. Close valve after each use and when empty. Use in accordance with Material Safety
Data Sheet.
Part #DB-USP
Printed by ratermann MFG inc.

GENERAL WARNINGS AND PRECAUTIONS

DO NOT REMOVE LABEL

Rx ONLY